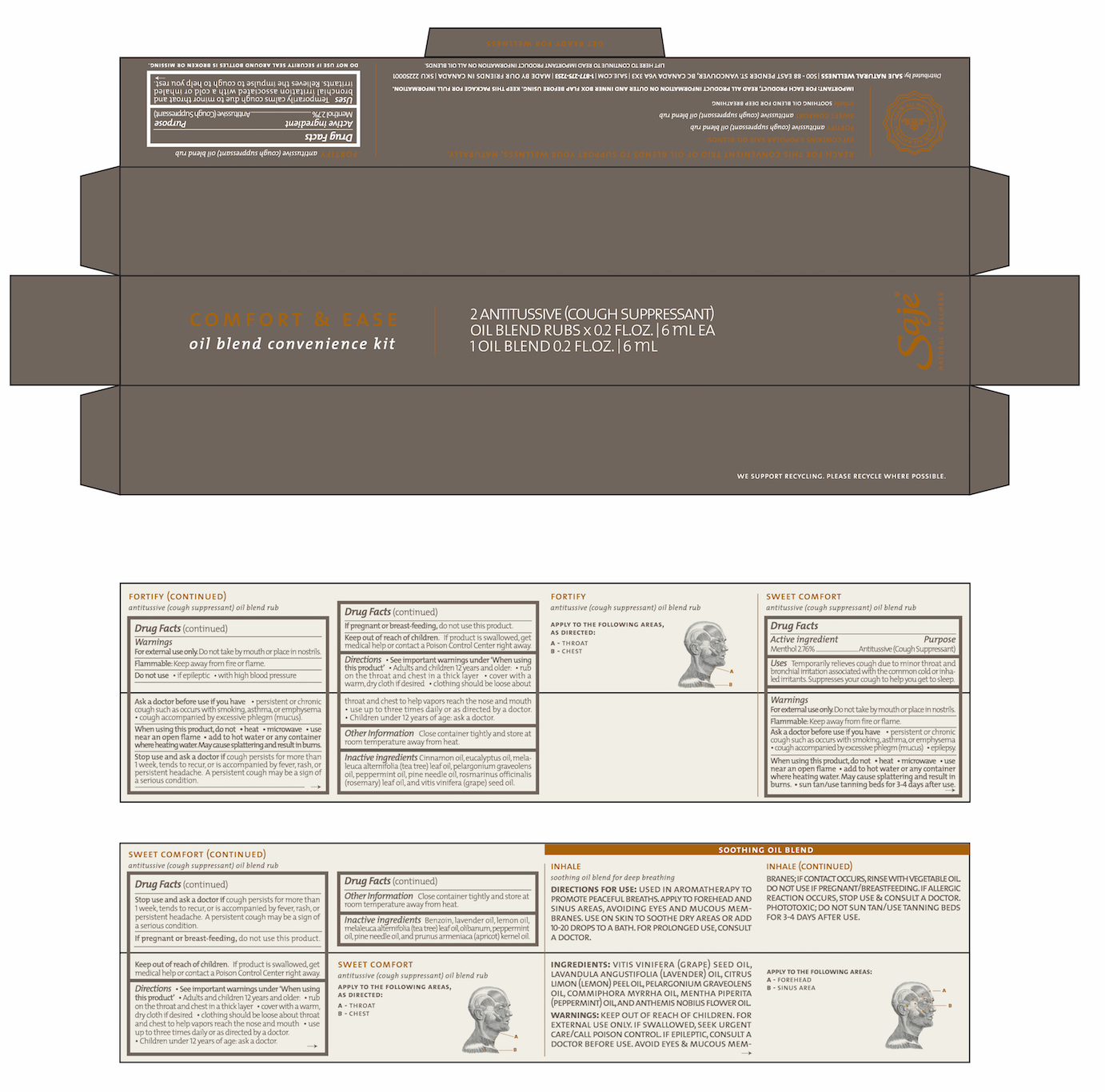 DRUG LABEL: Comfort and Ease
NDC: 70983-016 | Form: KIT | Route: TOPICAL
Manufacturer: Saje Natural Business Inc.
Category: otc | Type: HUMAN OTC DRUG LABEL
Date: 20161011

ACTIVE INGREDIENTS: MENTHOL 24.03 mg/1 mL; MENTHOL 24.56 mg/1 mL
INACTIVE INGREDIENTS: CINNAMON OIL; EUCALYPTUS OIL; TEA TREE OIL; PELARGONIUM GRAVEOLENS FLOWER OIL; PEPPERMINT OIL; PINE NEEDLE OIL (PINUS SYLVESTRIS); ROSEMARY OIL; GRAPE SEED OIL; STYRAX BENZOIN RESIN; LAVENDER OIL; LEMON OIL; TEA TREE OIL; FRANKINCENSE OIL; PEPPERMINT OIL; PINE NEEDLE OIL (PINUS SYLVESTRIS); APRICOT KERNEL OIL

Comfort and Ease Oil Blend Convenience Kit (3 x 6 ml)

GET READY FOR WELLNESS

Reach for this convenient trio of oil blends to support your wellness, naturally.

Kit Contains 3 popular saje oil blends:

FORTIFY antitussive (cough suppressant) oil blend rub

SWEET COMFORT antitussive (cough suppressant) oil blend rub

inhale SOOTHING OIL BLEND FOR DEEP BREATHING

IMPORTANT: FOR EACH PRODUCT, READ ALL PRODUCT INFORMATION ON OUTER AND INNER BOX FLAP BEFORE USING. KEEP THIS PACKAGE FOR FULL INFORMATION.

Distributed by: SAJE NATURAL WELLNESS | 500-88 E. Pender St. Vancouver, BC Canada, V6A 3X3 | saje.com | 1-877-275-7253 | Made by our friends in Canada

LIFT HERE TO CONTINUE TO READ IMPORTANT PRODUCT INFORMATION ON ALL OIL BLENDS

DO NOT USE IF SECURITY SEAL AROUND BOTTLES IS BROKEN OR MISSING.

We support recycling. Please recycle where possible

SKU 22250001

FORTIFY antitussive (cough suppressant) oil blend rub Drug Facts Active ingredient

Menthol 2.7%

Purpose Antitussive (Cough Suppressant)

Uses Temporarily calms cough due to minor throat and bronchial irritation associated with a cold or inhaled irritants. Relieves the impulse to cough to help you rest.

Warnings

For external use only. Do not that by mouth or place in nostrils.

Flammable. Keep away from fire or flame

Do not use

- if epileptic
- with high blood pressure

Ask doctor before use if you have

- persistent or chronic cough such as occurs with smoking, asthma, or emphysema
- cough accompanied by excessive phlegm (mucus).

When using this product, do not

- heat
- microwave
- use near an open flame
- add to hot water or any container where heating water. May cause splattering and result in burns.

Stop use and ask a doctor if

- cough persists for more than 1 week, tends to recur, or is accompanied by fever, rash, or persistent headache. A persistent cough may be a sign of a serious condition.

If pregnant or breast-feeding,

do not use this product.

Keep out of reach of children.

If product is swallowed, get medical help or contact a Poison Control Center right away.

Directions

- See important warnings under 'When using this product'
- Adults and children 12 years or older:
- rub on throat and chest in a thick layer
- cover with warm cloth if desired
- clothing should be loose about throat and chest to help vapors reach the nose and mouth

DOSAGE AND ADMINISTRATION

- use up to three times daily or as directed by a doctor
- Children under 12 years of age: ask a doctor.

Other information

Close container tightly and store at room temperature away from heat .

Inactive ingredients

Cinnamon oil, eucalyptus oil, melaleuca alternifolia (tea tree) leaf oil, pelargonium graveolens oil, peppermint oil, pine needle oil, rosmarinus officinalis (rosemary) leaf oil, and vitis vinifera (grape) seed oil.

Fortify antitussive (cough suppressant) oil blend rub

Apply to the following areas, as directed:

A - Throat

B - Chest

SWEET COMFORT antitussive (cough suppressant) oil blend rub Drug Facts Active ingredient

Menthol 2.76%

Purpose Antitussive (Cough Suppressant)

Uses Temporarily relieves cough due to minor throat and bronchial irritation associated with the common cold or inhaled irritants. Suppresses your cough to help you get to sleep.

Warnings

For external use only. Do not take by mouth or place in nostrils.

Flammable. Keep away from fire or flame.

Ask doctor before use if you have

- persistent or chronic cough such as occurs with smoking, asthma, or emphysema
- cough accompanied by excessive phlegm (mucus)
- epilepsy

When using this product, do not

- heat
- microwave
- use near an open flame
- add to hot water or any container where heating water. May cause splattering and result in burns.
- sun tan/use tanning beds for 3-4 days after use

Stop use and ask a doctor if

cough persists for more than 1 week, tends to recur, or is accompanied by fever, rash, or persistent headache. A persistent cough may be a sign of a serious condition

If pregnant of breast-feeding,

do not use this product.

Keep out of reach of children.

If product is swallowed, get medical help or contact a Poison Control Center right away.

Directions

- See important warnings under 'When using this product'
- Adults and children 12 years and older:
- rub on the throat and chest in a thick layer
- cover with a warm, dry cloth if desired
- clothing should be loose about throat and chest to help vapors reach the nose and mouth

DOSAGE AND ADMINISTRATION

- use up to three times daily or as directed by a doctor.
- Children under 12 years of age: ask a doctor.

Other information

- Close container tightly and store at room temperature away from heat.

Inactive ingredients

Benzoin, lavender oil, lemon oil, melaleuca alternifolia (tea tree) leaf oil, olibanum, peppermint oil, pine needle oil, and prunus armeniaca (apricot) kernel oil

Sweet Comfort antitussive (cough suppressant) oil blend rub

Apply to the following areas, as directed:

A - Throat

B - Chest

SOOTHING OIL BLEND INHALE soothing oil blend for deep breathing

Directions for use: Used in aromatherapy to promote peaceful breaths. Apply to forehead and sinus areas, avoiding eyes and mucous membranes. Use on skin to soothe dry areas or add 10-20 drops to a bath. For prolonged use, consult a doctor.

Ingredients: Vitis vinifera (grape) seed oil, lavandula angustifolia (lavender) oil, citrus limon (lemon) peel oil, pelargonium graveolens oil, commiphora myrrha oil, mentha piperita (peppermint) oil, and anthemis nobilis flower oil.

Warnings: Keep out of reach of children. For external use only. if swallowed, seek urgent care/call poison control. If epileptic, consult a doctor before use. Avoid eyes & mucous membranes; if contact occurs, rinse with vegetable oil. Do not use if pregnant/breastfeeding. If allergic reaction occurs, stop use & consult a doctor. Phototoxic; do not sun tan/use tanning beds for 3-4 days after use.

Apply to the following areas:

A - Forehead

B - Sinus Area

PACKAGE LABEL

COMFORT & EASE
oil blend convenience kit

2 ANTITUSSIVE (COUGH SUPPRESSANT) OIL BLEND RUBS X 0.2 FL. OZ. | 6 mL EA

1 OIL BLEND 0.2 FL. OZ. | 6 mL

Saje® Natural Wellness